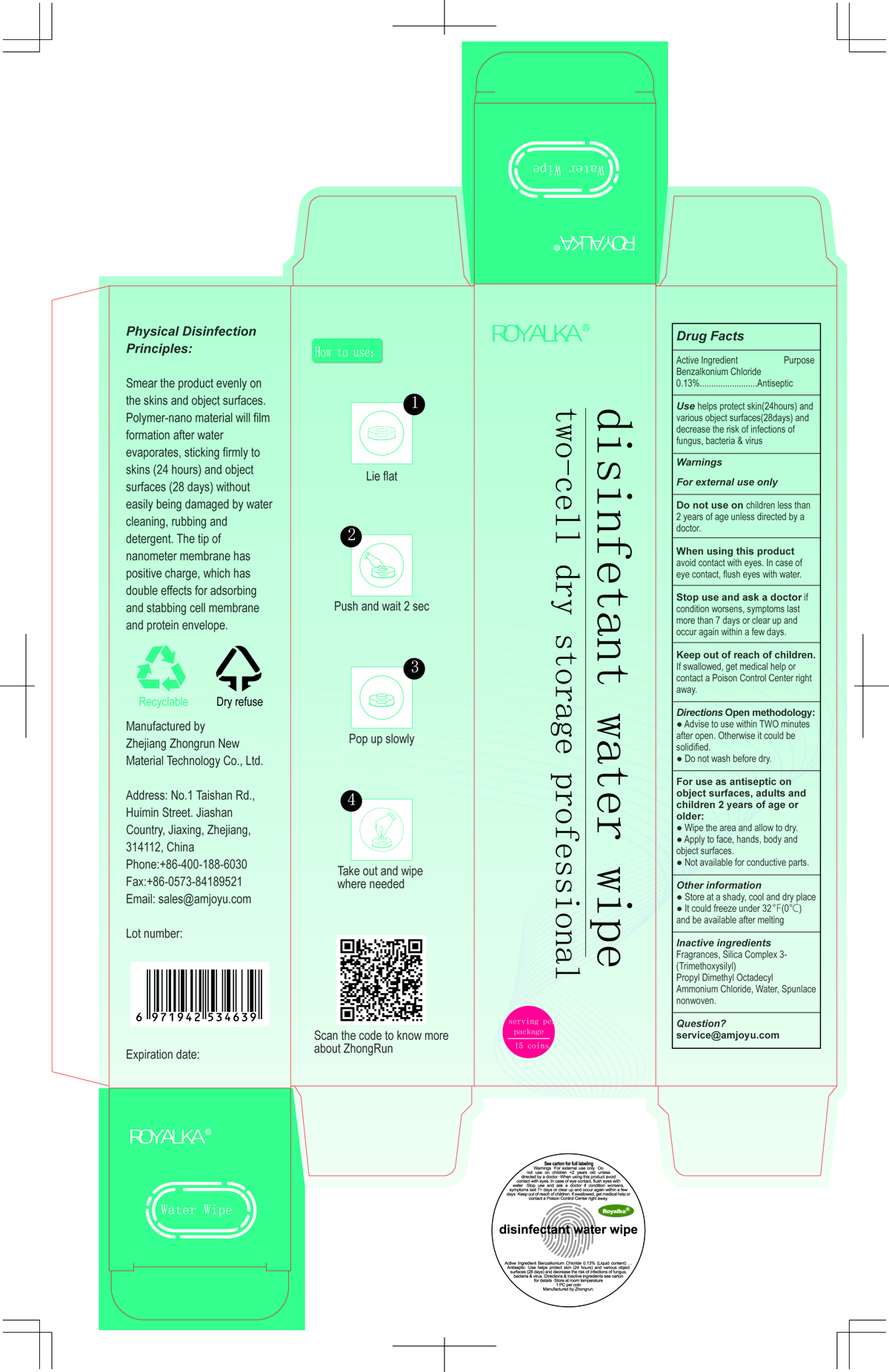 DRUG LABEL: Two-bin dry storage professional disinfectant water wipe
NDC: 77324-001 | Form: CLOTH
Manufacturer: Zhejiang Zhongrun New Material Technology Co., Ltd.
Category: otc | Type: HUMAN OTC DRUG LABEL
Date: 20200505

ACTIVE INGREDIENTS: BENZALKONIUM CHLORIDE 0.13 g/100 g
INACTIVE INGREDIENTS: DIMETHYLOCTADECYL(3-(TRIMETHOXYSILYL)PROPYL)AMMONIUM CHLORIDE; WATER

Two-bin dry storage professional disinfectant water wipe

Active Ingredient(s)

Benzalkonium Chloride 0.13%. Purpose: Antiseptic

Purpose

Antiseptic

Use

help protect skin (24 hours) and various object surfaces (28 days) and decrease the risk of infections of fungus, bacteria & virus

Warnings

For external use only.

Do not use

on children less than 2 years of age unless directed by a doctor.

When using this prodcut

avoid contact with eyes. In case of eye contact, flush eyes with water.

Stop use and ask a doctor

if condition worsens, symptoms last more than 7 days or clear up and occur again within a few days.

Keep out of reach of children. If swallowed, get medical help or contact a Poison Control Center right away.

Directions

Open methodology:

- Advise to use within TWO minutes after open. Otherwise it could be solidified.
- Do not wash before day.

For use as antiseptic on object surfaces, adults and children 2 years of age or older

- Wipe the area and allow to dry.
- Apply to face, hands, body and object surfaces.
- Not available for conductive parts.

Other information

- Store at a shady, cool and dry place.
- It could freeze under 32F (0C) and be available after melting.

Inactive ingredients

Silica Complex 3-(Trimethoxysilyl) Propyl Dimethyl Octadecyl Ammonium Chloride), Water

Package Label - Principal Display Panel

NDC: 77324-001-01